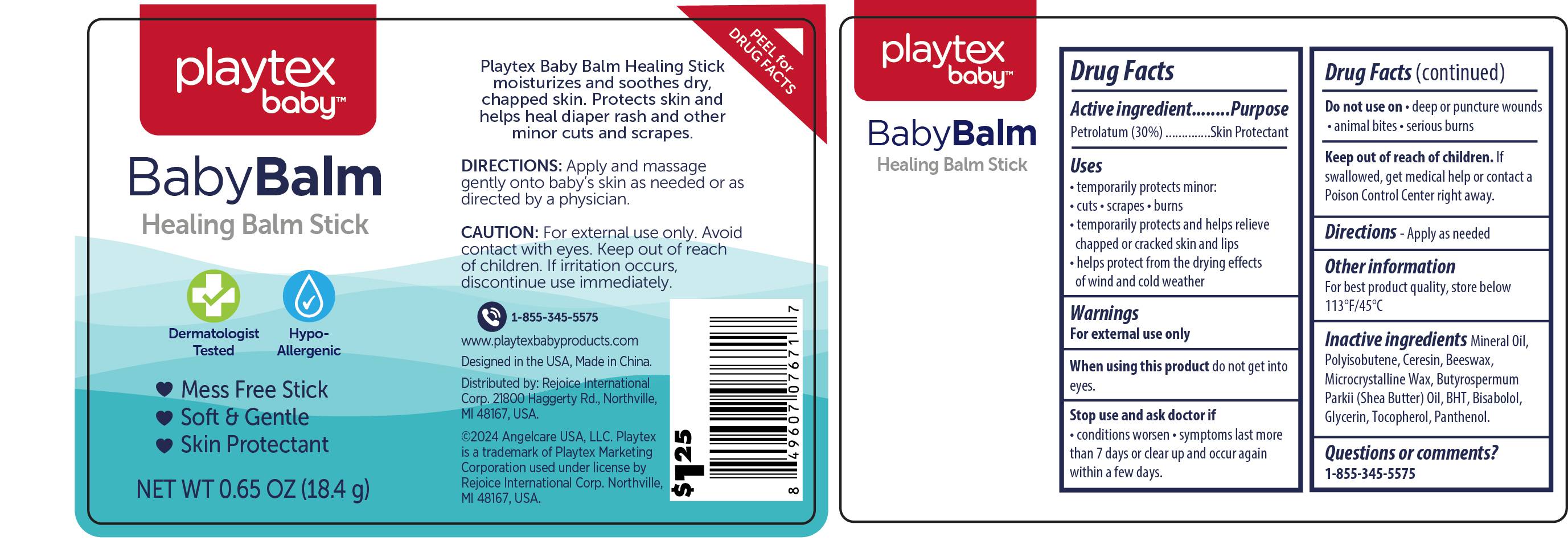 DRUG LABEL: Baby Balm Stick 0.65oz
NDC: 58503-203 | Form: OINTMENT
Manufacturer: China Ningbo Shangge Cosmetics Technology Corp.
Category: otc | Type: HUMAN OTC DRUG LABEL
Date: 20240910

ACTIVE INGREDIENTS: PETROLATUM 30 g/100 g
INACTIVE INGREDIENTS: BUTYLATED HYDROXYTOLUENE; PANTHENOL; POLYISOBUTYLENE (1300 MW); MICROCRYSTALLINE WAX; CERESIN; YELLOW WAX; TOCOPHEROL; LEVOMENOL; SHEANUT OIL; GLYCERIN; MINERAL OIL

Active ingredient

Petrolatun 30%

Purpose

Skin Protectant (Ointment)

Use

temporarily protects minor;
cut
scrapes
burns
temporarily protects and helps relieve chapped or cracked skin and lips
helps protect from the drying effects of wind and cold weather

Warnings

For external use only

When using this product do not get into eyes.

Stop use and ask a doctor if

condition worsens
symptoms last more than 7days or clear up and occur again within a few days.

Do not use on

deep or puncture wounds
animal bites
serious burns

Keep out of reach of children

If swallowed, get medical help or contact a Poison Control Center right away.

Directions

Apply as needed.

Inactive ingredients

Mineral Oil
polyisobutene
polyisobutene
beeswax
microcrystalline wax
butyrospermum parkii (shea butter) oil
BHT
Bisabolol
Glycerin
Tocopherol
Panthenol

Other information

For best product quality, store below 113°F/45°C.